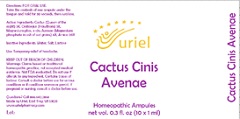 DRUG LABEL: Cactus Cinis Avenae
NDC: 48951-3239 | Form: LIQUID
Manufacturer: Uriel Pharmacy Inc.
Category: homeopathic | Type: HUMAN OTC DRUG LABEL
Date: 20201218

ACTIVE INGREDIENTS: MAGNESIUM PHOSPHATE, TRIBASIC, PENTAHYDRATE 6 [hp_X]/1 mL; SELENICEREUS GRANDIFLORUS STEM 3 [hp_X]/1 mL; HAWTHORN LEAF WITH FLOWER 3 [hp_X]/1 mL; ARNICA MONTANA FLOWER 20 [hp_X]/1 mL
INACTIVE INGREDIENTS: LACTOSE, UNSPECIFIED FORM; SODIUM CHLORIDE; WATER

Cactus Cinis Avenae

INDICATIONS AND USAGE

Directions: FOR ORAL USE.

DOSAGE AND ADMINISTRATION

Take the contents of one ampule under the tongue and hold for 30 seconds, then swallow.

ACTIVE INGREDIENT

Active Ingredients: Cactus (Queen of the night) 3X, Crataegus (Hawthorn) 3X,Magnesium phos. e cin. Avenae (Magnesium phosphate in ash of oat grains) 6X, Arnica 20X

Inactive Ingredients: Water, Salt, Lactose

PURPOSE

Use: Temporary relief of headache.

KEEP OUT OF REACH OF CHILDREN.

WARNINGS

Warnings: Claims based on traditional homeopathic practice, not accepted medical evidence. Not FDA evaluated. Do not use if allergic to any ingredient. Contains traces of lactose. Consult a doctor before use for serious conditions or if conditions worsen or persist. If pregnant or nursing, consult a doctor before use.

Questions? Call 866.642.2858
Made by Uriel, East Troy, WI 53120
www.urielpharmacy.com